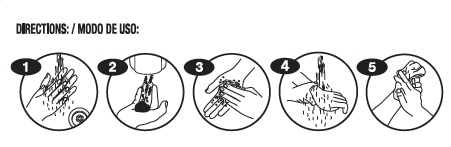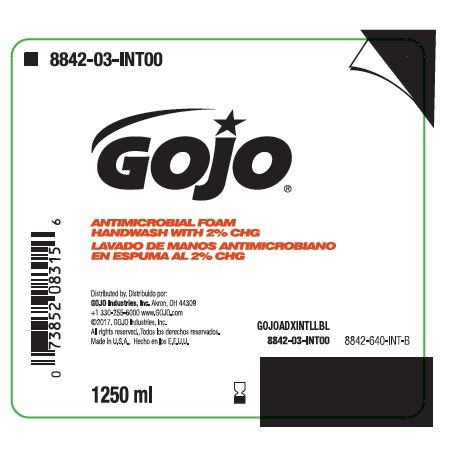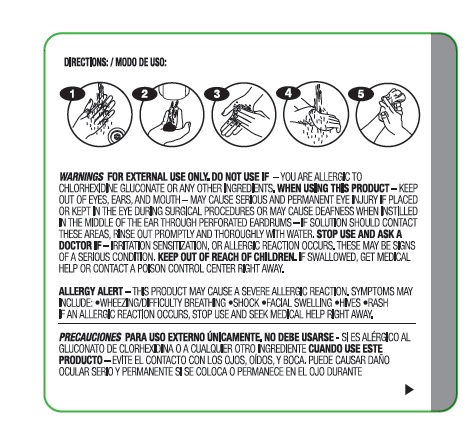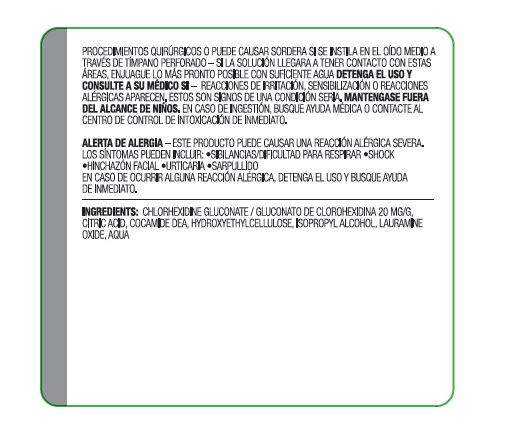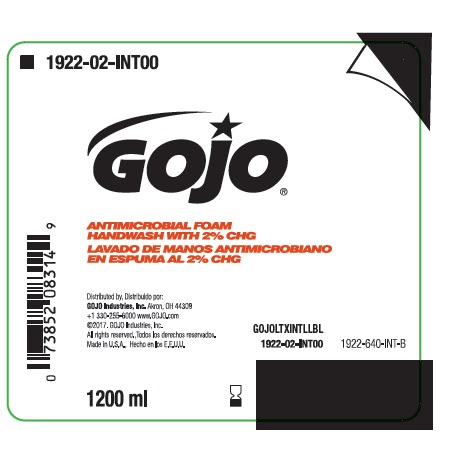 DRUG LABEL: Antimicrobial Foam Handwash
NDC: 21749-416 | Form: LIQUID
Manufacturer: GOJO Industries, Inc.
Category: otc | Type: HUMAN OTC DRUG LABEL
Date: 20180824

ACTIVE INGREDIENTS: CHLORHEXIDINE GLUCONATE 20 mg/1 mL
INACTIVE INGREDIENTS: WATER; ISOPROPYL ALCOHOL; CITRIC ACID MONOHYDRATE; HYDROXYETHYL CELLULOSE (2000 CPS AT 1%); LAURAMINE OXIDE

GOJO International

PURPOSE

Antiseptic

Warnings/Precauciones

For external use only

Allergy Alert:

This product may cause a severe allergic reaction. Symptoms may include:

- wheezing/difficulty breathing
- shock
- facial swelling
- hives
- rash

If an allergic reaction occurs, stop use and seek medical help right away

Para Use Externo Únicamente

Alerta De Allergia:

Este producto puede causar un reacción alérgica severa. Los síntomas pueden incluir:

- sibilancias/dificultad para respirar
- shock
- hinchazón facial
- urticaria
- sarpullido

En caso de ocurrir alguna reacción alérgica, detenga el uso y busque ayuda de inmediato

Do not use/No debe usante

If you are allergic to chlorhexidine gluconate or any other ingredients

Si es alérgico al gluconato de chlorhexidina o a cualquier otro ingrediente

When using this product/ Cuando use este producto

Keep out of eyes, ear and mouth. May cause serious and permenant eye injury if placed or kept in the eye during surgical procedures or may cause deafness when instilled in the middle of the ear through perforated eardrums. If solution should contact these areas, rinse out promptly and thoroughly with water.

Evite el contacto con los ojos, oídos, y boca. Puede causar daño ocular serio y permanente si se coloca o permanece en el ojo durante procedimientos quirúrgicos o puede causar sordera si se instila en el oído medio a través de tímpano perforado. Si la solución llegara a tener contacto con estas àreas, enjuague lo más pronto posible con suficiente agua.

Stop use an ask a doctor if/ Mantengase fuera consulte a su médico si

Irrititation, sensitization or allergic reaction occurs. These may be signs of a serious condition.

Reacciones de irritación, sensibilización o reacciones alérgicas aparecen. Estos son signos de una condicíon seria.

Keep out of reach of children

If swallowed, get medical help or contact a poison control center right away.

En caso de ingestión, busque ayuda médica o contacte al centro de control de intoxicación de inmediato.

ACTIVE INGREDIENT

Chlorhexidine Gluconate/Gluconato de chlorhexidina 20 MG/G

INACTIVE INGREDIENT

Citric acid, cocamide DEA, hydroxyethlycellulose, isopropyl alcohol, lauramine oxide, aqua

INDICATIONS AND USAGE

Antimicrobial Handwash

PACKAGE LABEL

Chlorhexidine Gluconate 2% Solution

NDC 21749-416-89

GOJO Industries, Inc

Akron, OH 44309

+330 255-6000

www.GOJO.com

GOJOLTXINTLLBL

Net Wt 1200 mL

Chlorhexidine Gluconate 2% Solution

NDC 21749-416-90

GOJO Industries, Inc

Akron, OH 44309

+330 255-6000

www.GOJO.com

GOJOADXINTLLBL

Net Wt 1250 mL